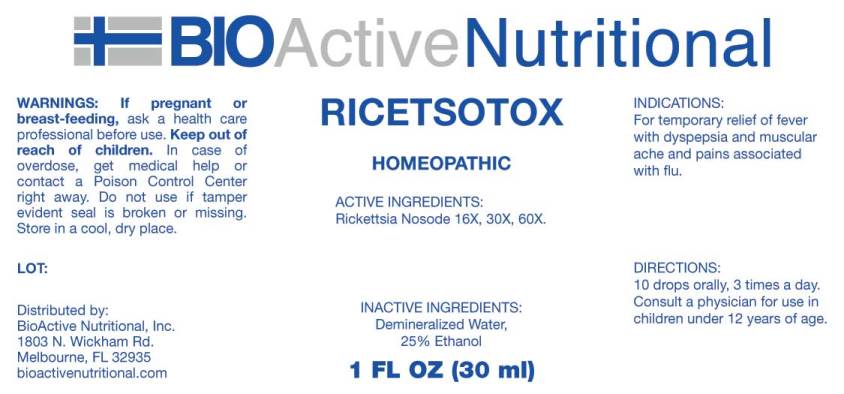 DRUG LABEL: Ricetsotox
NDC: 43857-0452 | Form: LIQUID
Manufacturer: BioActive Nutritional, Inc.
Category: homeopathic | Type: HUMAN OTC DRUG LABEL
Date: 20170619

ACTIVE INGREDIENTS: RICKETTSIA PROWAZEKII 16 [hp_X]/1 mL
INACTIVE INGREDIENTS: WATER; ALCOHOL

Drug Facts:

ACTIVE INGREDIENTS:

Rickettsia Nosode 16X, 30X, 60X.

INDICATIONS:

For temporary relief of fever with dyspepsia and muscular ache and pains associated with flu.

WARNINGS:

If pregnant or breast-feeding, ask a health care professional before use.

Keep out of reach of children. In case of overdose, get medical help or contact a Poison Control Center right away.

Do not use if tamper evident seal is broken or missing. Store in a cool, dry place.

Keep out of reach of children. In case of overdose, get medical help or contact a Poison Control Center right away.

DIRECTIONS:

10 drops orally, 3 times a day. Consult a physician for use in children under 12 years of age.

INDICATIONS:

For temporary relief of fever with dyspepsia and muscular ache and pains associated with flu.

INACTIVE INGREDIENTS:

Demineralized Water, 25% Ethanol

QUESTIONS:

Distributed by:

BioActive Nutritional, Inc.

1803 N. Wickham Rd.

Melbourne, FL 32935

PACKAGE LABEL DISPLAY:

BIOActive Nutritional

RICETSOTOX

HOMEOPATHIC

1 FL OZ (30 ml)